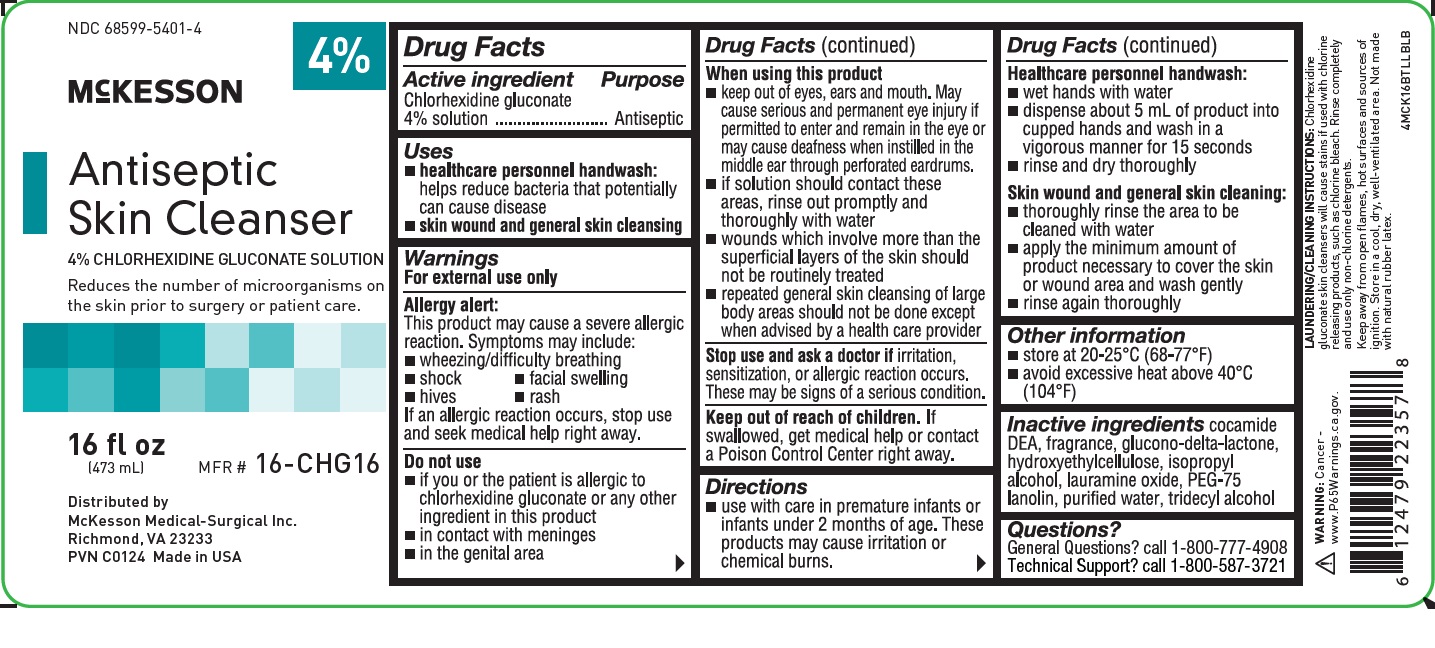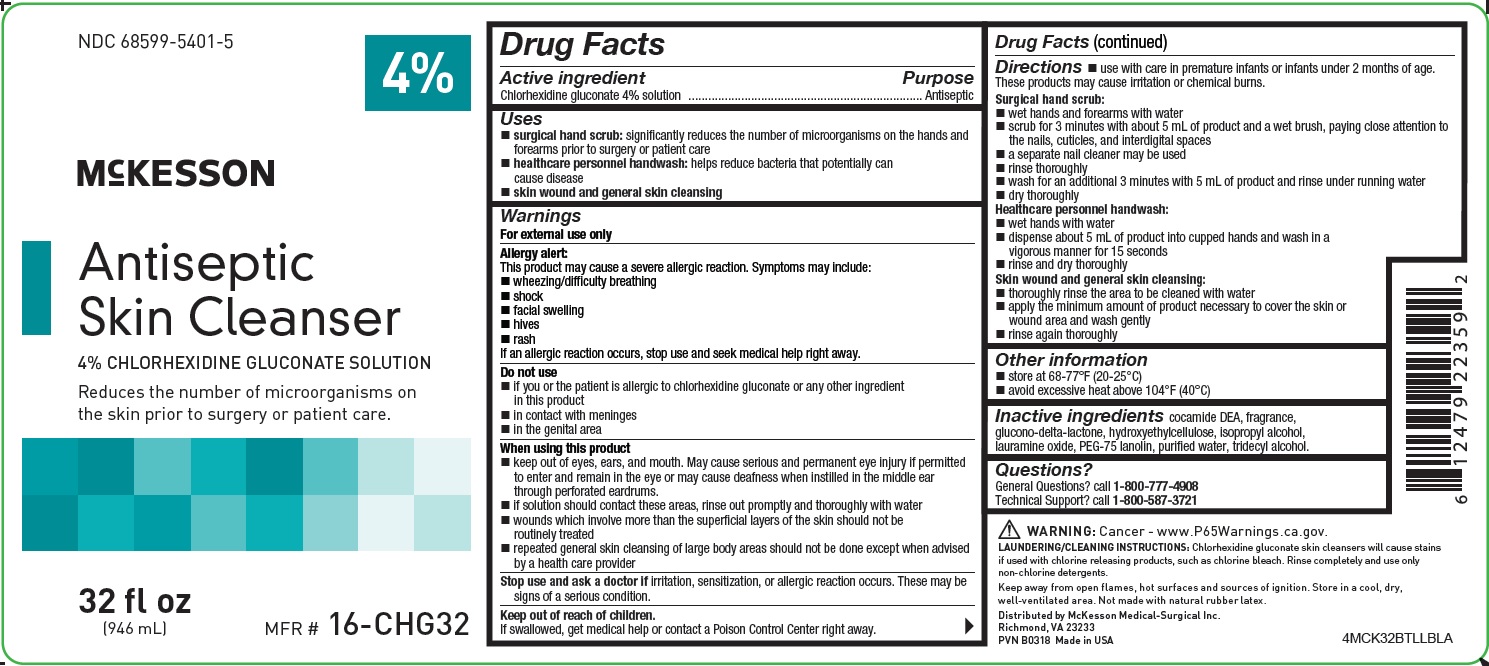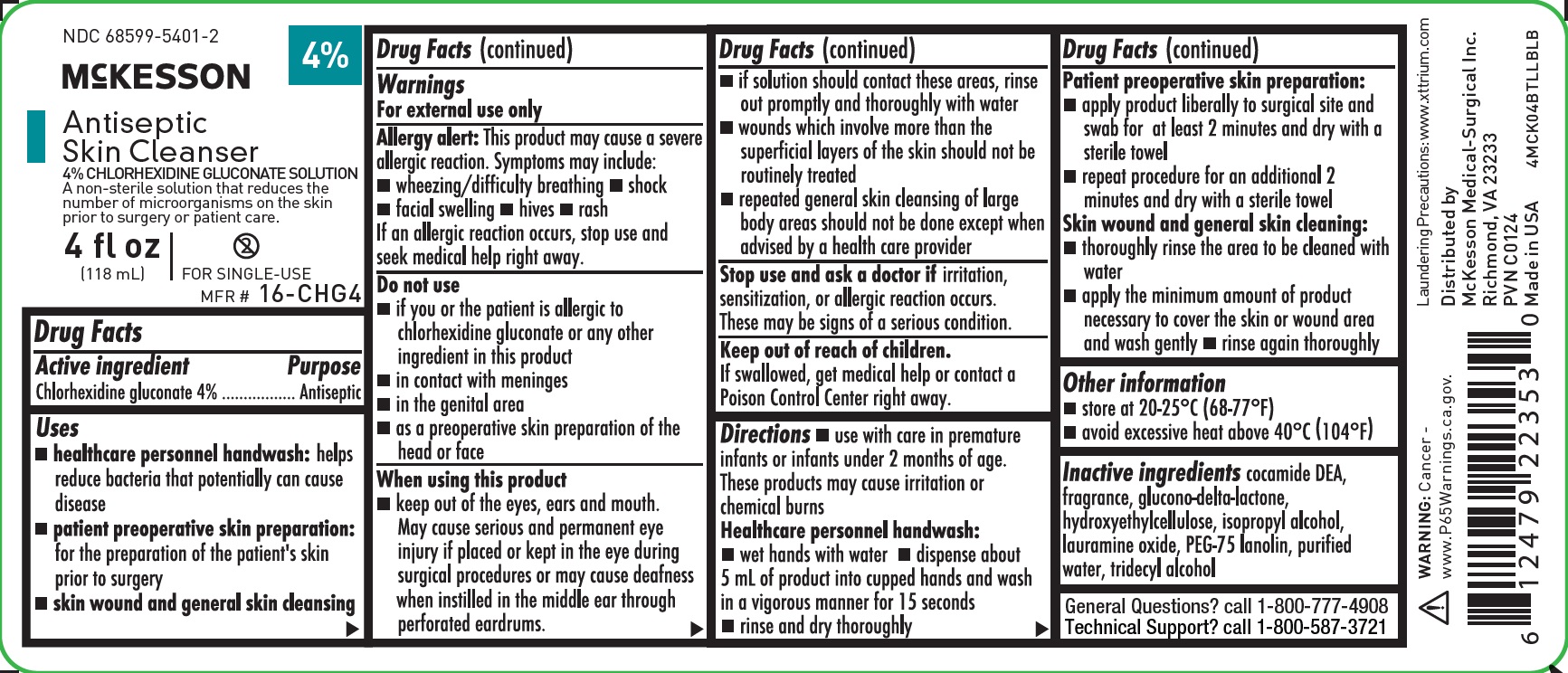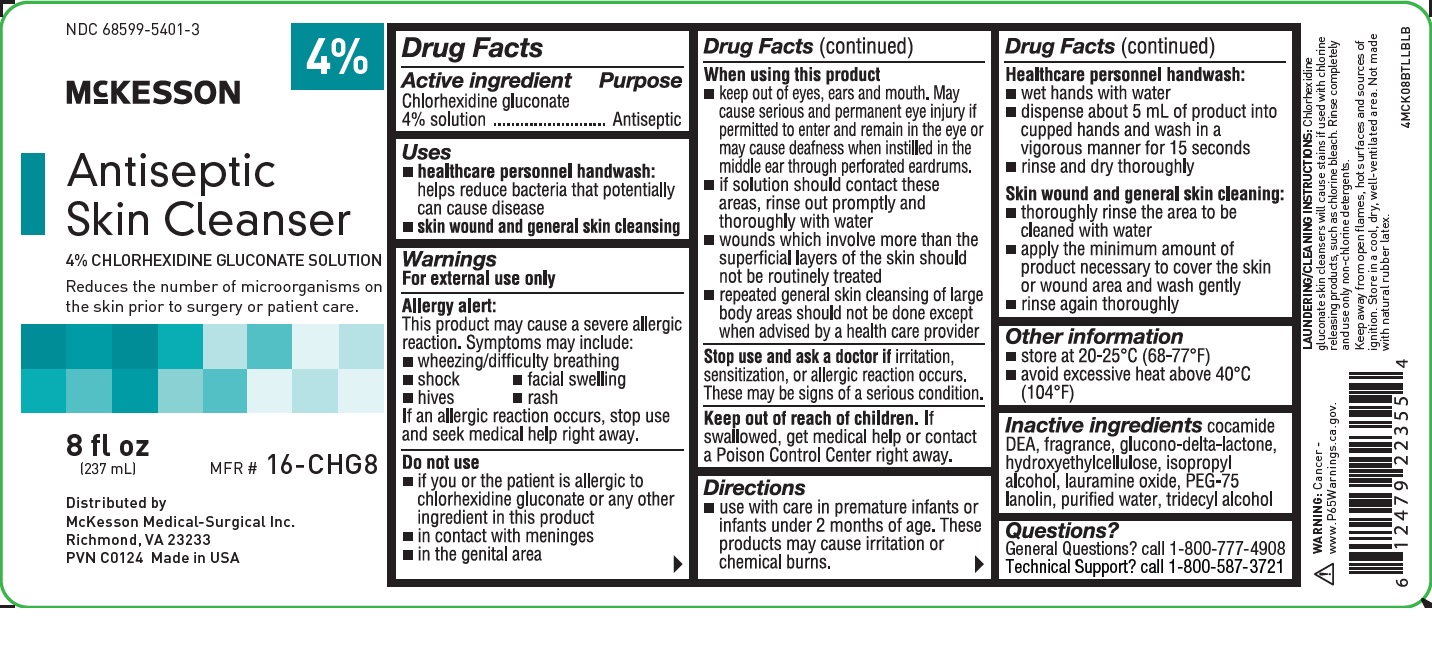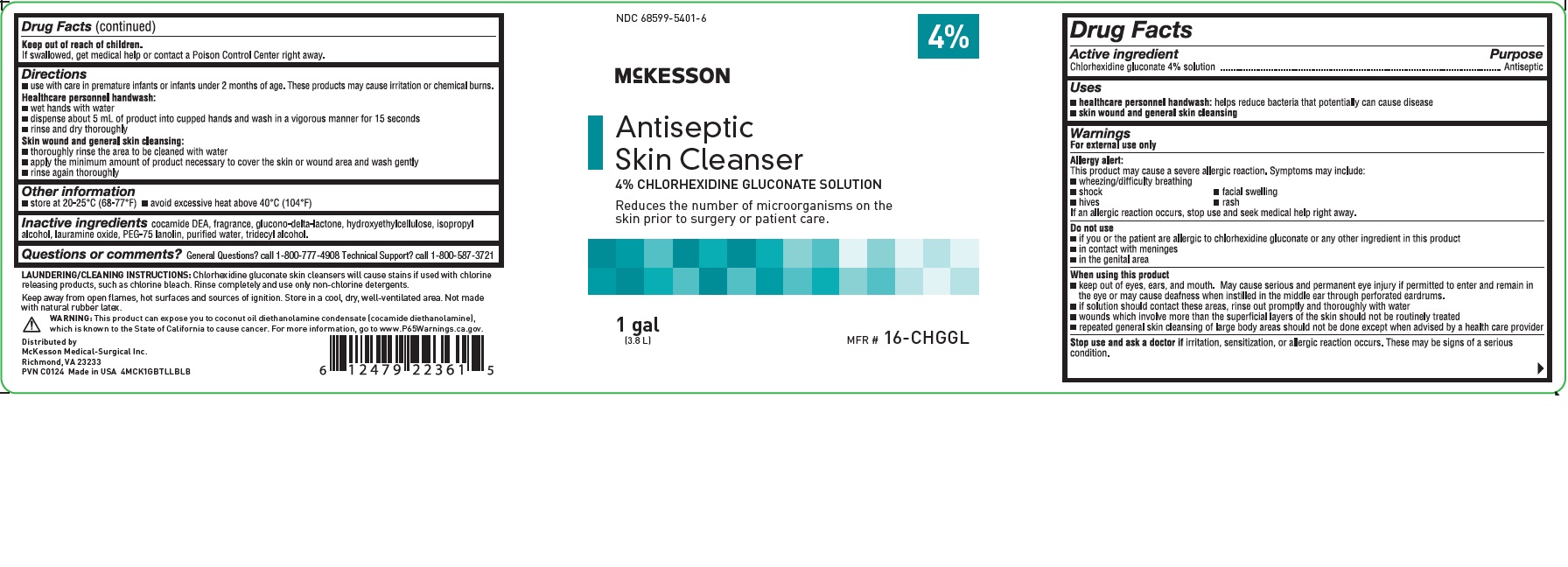 DRUG LABEL: Antiseptic Skin Cleanser
NDC: 68599-5401 | Form: SOLUTION
Manufacturer: McKesson Medical-Surgical
Category: otc | Type: HUMAN OTC DRUG LABEL
Date: 20250116

ACTIVE INGREDIENTS: CHLORHEXIDINE GLUCONATE 4 g/100 mL
INACTIVE INGREDIENTS: COCO DIETHANOLAMIDE; GLUCONOLACTONE; HYDROXYETHYL CELLULOSE (100 MPA.S AT 2%); ISOPROPYL ALCOHOL; LAURAMINE OXIDE; PEG-75 LANOLIN; WATER; TRIDECYL ALCOHOL

Antiseptic Skin Cleanser

Active ingredient

Chlorhexidine gluconate 4% solution

Purpose

Antiseptic

Uses

- surgical hand scrub: significantly reduces the number of microorganisms on the hands and forearms prior to surgery or patient care
- healthcare personnel handwash:helps reduce bacteria that potentially can cause disease
- patient preoperative skin preparation:for the preparation of the patient's skin prior to surgery
- skin wound and general skin cleansing

Warnings

For external use only

Allergy Alert

This product may cause a severe allergic reaction. Symptoms may include:

- wheezing/difficulty breathing
- shock
- facial swelling
- hives
- rash

If an allergic reaction occurs, stop use and seek medical help right away.

Do not use

- if you are allergic to chlorhexidine gluconate or any other ingredients in this product
- in contact with meninges
- in the genital area
- as a preoperative skin preparation of the head or face

When using this product

- keep out of eyes, ears, and mouth. May cause serious and permanent eye injury if placed or kept in the eye during surgical procedures or may cause deafness when instilled in the middle ear through perforated eardrums
- if solution should contact these areas, rinse out promptly and thoroughly with water
- wounds which involve more than the superficial layers of the skin should not be routinely treated
- repeated general skin cleansing of large body areas should not be done except when the underlying condition makes it necessary to reduce the bacterial population of the skin

Stop use and ask doctor ifirritation, sensitization or allergic reaction occurs. These may be signs of a serious condition.

Keep out of reach of children.If swallowed, get medical help or contact a Poison Control Center right away.

Directions

- use with care in premature infants or infants under 2 months of age. These products may cause irritation or chemical burns.

Healthcare personnel handwash:

- wet hands with water
- dispense about 5 mL of product into cupped hands and wash in a vigorous manner for 15 seconds
- rinse and dry thoroughly

Patient preoperative skin preparation:

- apply product liberally to surgical site and swab for at least 2 minutes and dry with a sterile towel
- repeat procedure for an additional 2 minutes and dry with a sterile towel

Skin wound and general skin cleaning:

- thoroughly rinse the area to be cleaned with water
- apply the minimum amount of product necessary to cover the skin or wound area and wash gently
- rinse again thoroughly

Other information

- store at 68-77ºF (20-25°C)
- avoid excessive heat above 104°F (40°C)

Inactive ingredients

cocamide DEA, fragrance, glucono-delta-lactone, hydroxyethylcellulose, isopropyl alcohol, lauramine oxide, PEG-75 lanolin, purified water, tridecyl alcohol

Questions?

General Questions? Call 1-800-777-4908

Technical Support? Call 1-800-587-3721

Principal Display Panel - McKesson Antiseptic Skin Cleanser 4 fl oz Bottle Label

NDC 68599-5401-2

4%

McKESSON

AntisepticSkin Cleanser

4% CHLORHEXIDINE GLUCONATE SOLUTION

Reduces the number of microorganisms on the skin prior to surgery or patient care.

4 fl oz
(118 mL)

DO NOT REUSE

MFR # 16-CHG4

Principal Display Panel - McKesson Antiseptic Skin Cleanser 8 fl oz Bottle Label

NDC 68599-5401-3

4%

McKESSON

Antiseptic Skin Cleanser

4% CHLORHEXIDINE GLUCONATE SOLUTION

Reduces the number of microorganisms on the skin prior to surgery or patient care.

8 fl oz
(237 mL)

MFR # 16-CHG8

Principal Display Panel - McKesson Antiseptic Skin Cleanser 16 fl oz Bottle Label

NDC 68599-5401-4

4%

McKESSON

Antiseptic Skin Cleanser

4% CHLORHEXIDINE GLUCONATE SOLUTION

Reduces the number of microorganisms on the skin prior to surgery or patient care.

16 fl oz

(473 mL)

MFR # 16-CHG16

Principal Display Panel - McKesson Antiseptic Skin Cleanser 32 fl oz Bottle Label

NDC 68599-5401-5

4%

McKESSON

Antiseptic Skin Cleanser

4% CHLORHEXIDINE GLUCONATE SOLUTION

Reduces the number of microorganisms on the skin prior to surgery or patient care.

32 fl oz
(946 mL)

MFR # 16-CHG32

Principal Display Panel - McKesson Antiseptic Skin Cleanser 1 gal Bottle Label

NDC 68599-5401-6

McKESSON

Antiseptic Skin Cleanser

4% CHLORHEXIDINE GLUCONATE SOLUTION

Reduces the number of microorganisms on the skin prior to surgery or patient care.

1 gal
(3.8 L)

MFR # 16-CHGGL